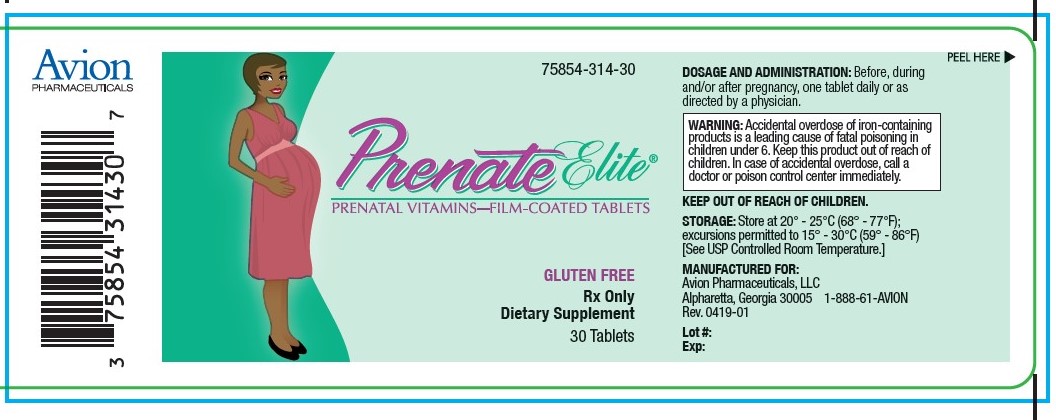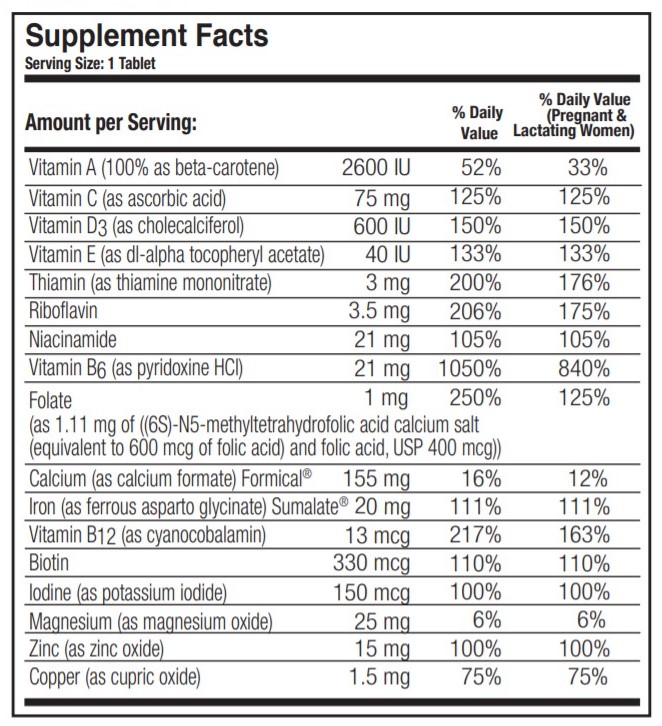 DRUG LABEL: Prenate Elite
NDC: 75854-314 | Form: TABLET, COATED
Manufacturer: Avion Pharmaceuticals, LLC
Category: prescription | Type: HUMAN PRESCRIPTION DRUG LABEL
Date: 20240123

ACTIVE INGREDIENTS: .BETA.-CAROTENE 2600 [iU]/1 1; ASCORBIC ACID 75 mg/1 1; CHOLECALCIFEROL 600 [iU]/1 1; .ALPHA.-TOCOPHEROL ACETATE, DL- 40 [iU]/1 1; THIAMINE MONONITRATE 3 mg/1 1; RIBOFLAVIN 3.5 mg/1 1; NIACINAMIDE 21 mg/1 1; PYRIDOXINE HYDROCHLORIDE 21 mg/1 1; FOLIC ACID 400 ug/1 1; 5-METHYLTETRAHYDROFOLIC ACID 600 ug/1 1; CALCIUM FORMATE 155 mg/1 1; FERROUS ASPARTO GLYCINATE 20 mg/1 1; CYANOCOBALAMIN 13 ug/1 1; BIOTIN 330 ug/1 1; POTASSIUM IODIDE 150 ug/1 1; MAGNESIUM OXIDE 25 mg/1 1; ZINC OXIDE 15 mg/1 1; CUPRIC OXIDE 1.5 mg/1 1
INACTIVE INGREDIENTS: POWDERED CELLULOSE; SILICON DIOXIDE; CROSCARMELLOSE SODIUM; STEARIC ACID; MAGNESIUM STEARATE; HYPROMELLOSES; TRIACETIN; TITANIUM DIOXIDE

PRENATE ELITE®

Rx Only Dietary Supplement

DESCRIPTION

DESCRIPTION: PRENATE ELITE® is a white, oval, oil- and water-soluble, multivitamin/multimineral, film-coated tablet debossed with “PN” on one side and blank on the other.

INACTIVE INGREDIENT

OTHER INGREDIENTS: Microcrystalline Cellulose, Silicon Dioxide, Croscarmellose Sodium, Stearic Acid, Magnesium Stearate, Film Coating (Hydroxypropyl Methylcellulose, Triacetin, Titanium Dioxide).

INDICATIONS AND USAGE

INDICATIONS: PRENATE ELITE® is a multivitamin/multimineral fatty acid dietary supplement indicated for use in improving the nutritional status of women throughout pregnancy and in the postnatal period for both lactating and nonlactating mothers.

CONTRAINDICATIONS

CONTRAINDICATIONS: PRENATE ELITE® is contraindicated in patients with a known hypersensitivity to any of the ingredients.

PRECAUTIONS

PRECAUTIONS: Folic acid alone is improper therapy in the treatment of pernicious anemia and other megaloblastic anemias where Vitamin B12 is deficient. Folic acid in doses above 1.0 mg daily may obscure pernicious anemia in that hematologic remission can occur while neurological manifestations progress.

BOXED WARNING

WARNING: Accidental overdose of iron-containing products is a leading cause of fatal poisoning in children under 6. Keep this product out of reach of children. In case of accidental overdose, call a doctor or poison control center immediately.

ADVERSE REACTIONS

ADVERSE REACTIONS: Allergic sensitization has been reported following both oral and parenteral administration of folic acid.

DOSAGE AND ADMINISTRATION: Before, during and/or after pregnancy, one tablet daily or as directed by a physician.

HOW SUPPLIED

HOW SUPPLIED: Bottles of 30 tablets (75854-314-30). The listed product number is not a National Drug Code. Instead, Avion Pharmaceuticals has assigned a product code formatted according to standard industry practice to meet the formatting requirements of pharmacy and healthcare insurance computer systems.

STORAGE AND HANDLING

Store at 20° - 25°C (68° - 77°F); excursions permitted to 15° - 30°C (59° - 86°F) [See USP Controlled Room Temperature.]

MANUFACTURED FOR:
Avion Pharmaceuticals, LLC
Alpharetta, Georgia 30005
1-888-61-AVION

Rev. 0519-01

Formical® is a registered trademark of Nephro-Tech 1, LLC, covered by one or more claims of U.S. Patent No. 6,528,542.

Sumalate® is a registered trademark of Albion Laboratories, Inc., covered by one or more claims of U.S. Patent Nos. 5,516,925, 6,716,814, 8,007,846, and 8,425,956.

PACKAGE LABEL.PRINCIPAL DISPLAY PANEL

75854-314-30

Prenate Elite®
PRENATAL VITAMINS-FILM-COATED TABLETS

GLUTEN FREE
Rx Only
Dietary Supplement

30 Tablets